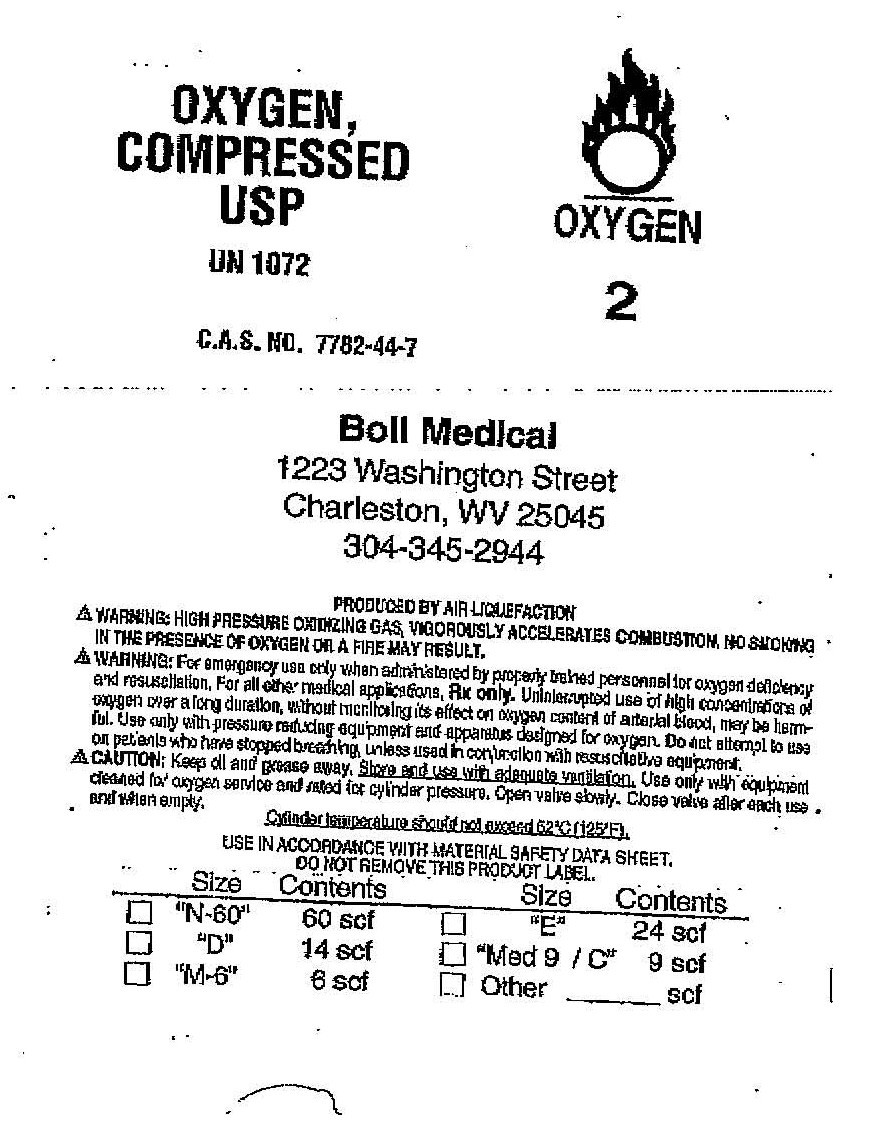 DRUG LABEL: Oxygen
NDC: 66497-0001 | Form: GAS
Manufacturer: Boll Medical Inc.
Category: prescription | Type: HUMAN PRESCRIPTION DRUG LABEL
Date: 20090911

ACTIVE INGREDIENTS: Oxygen 99 L/100 L

Oxygen